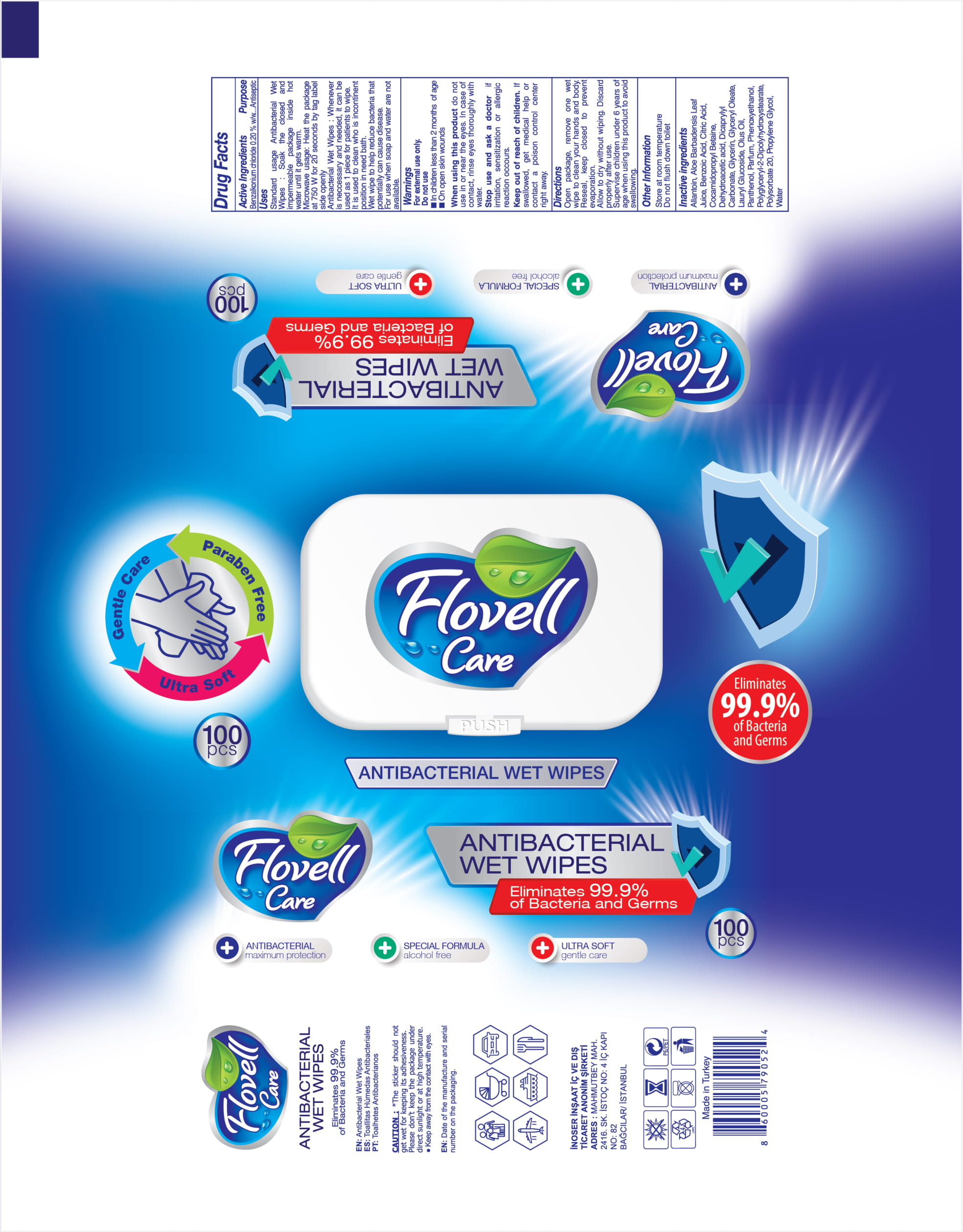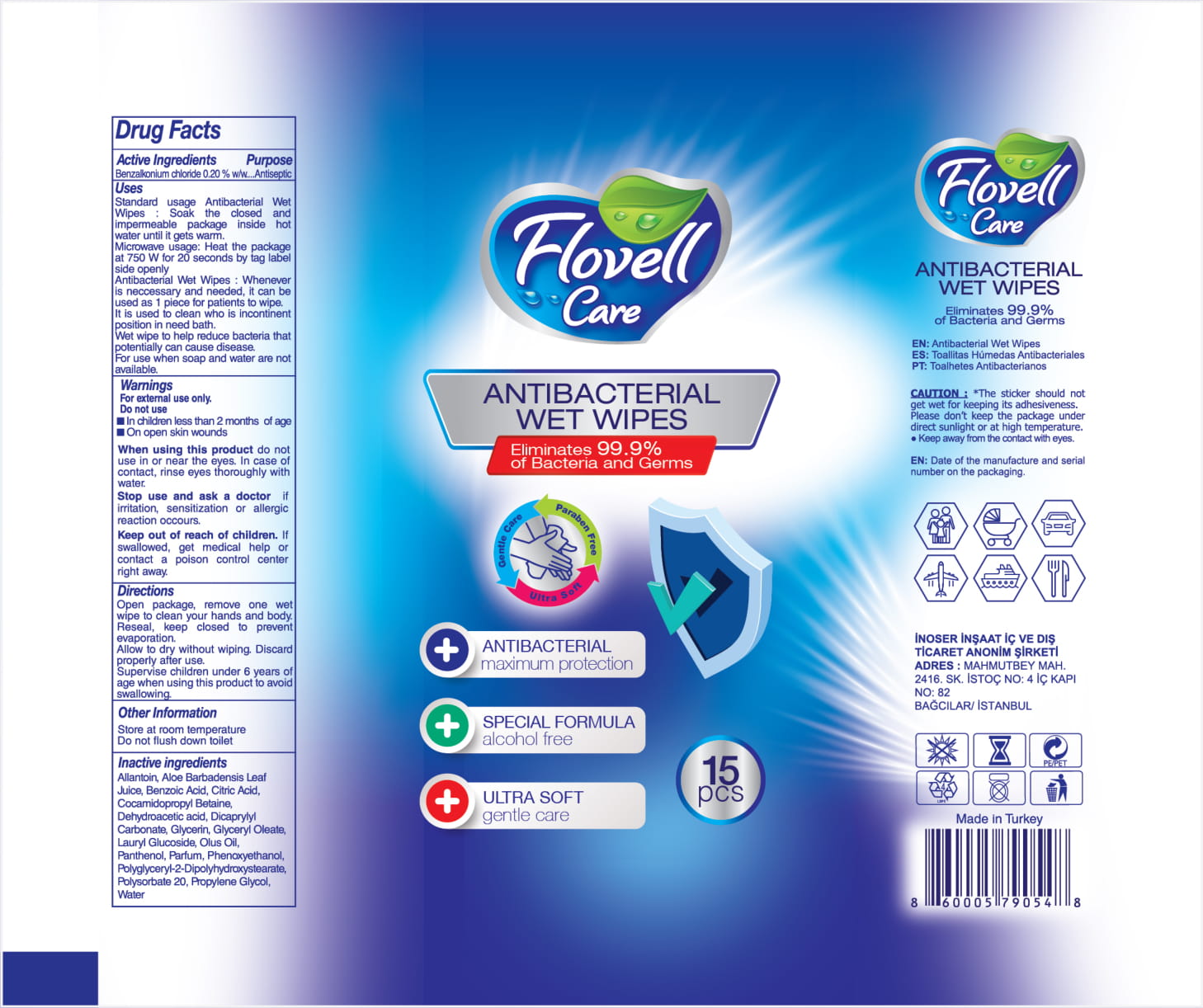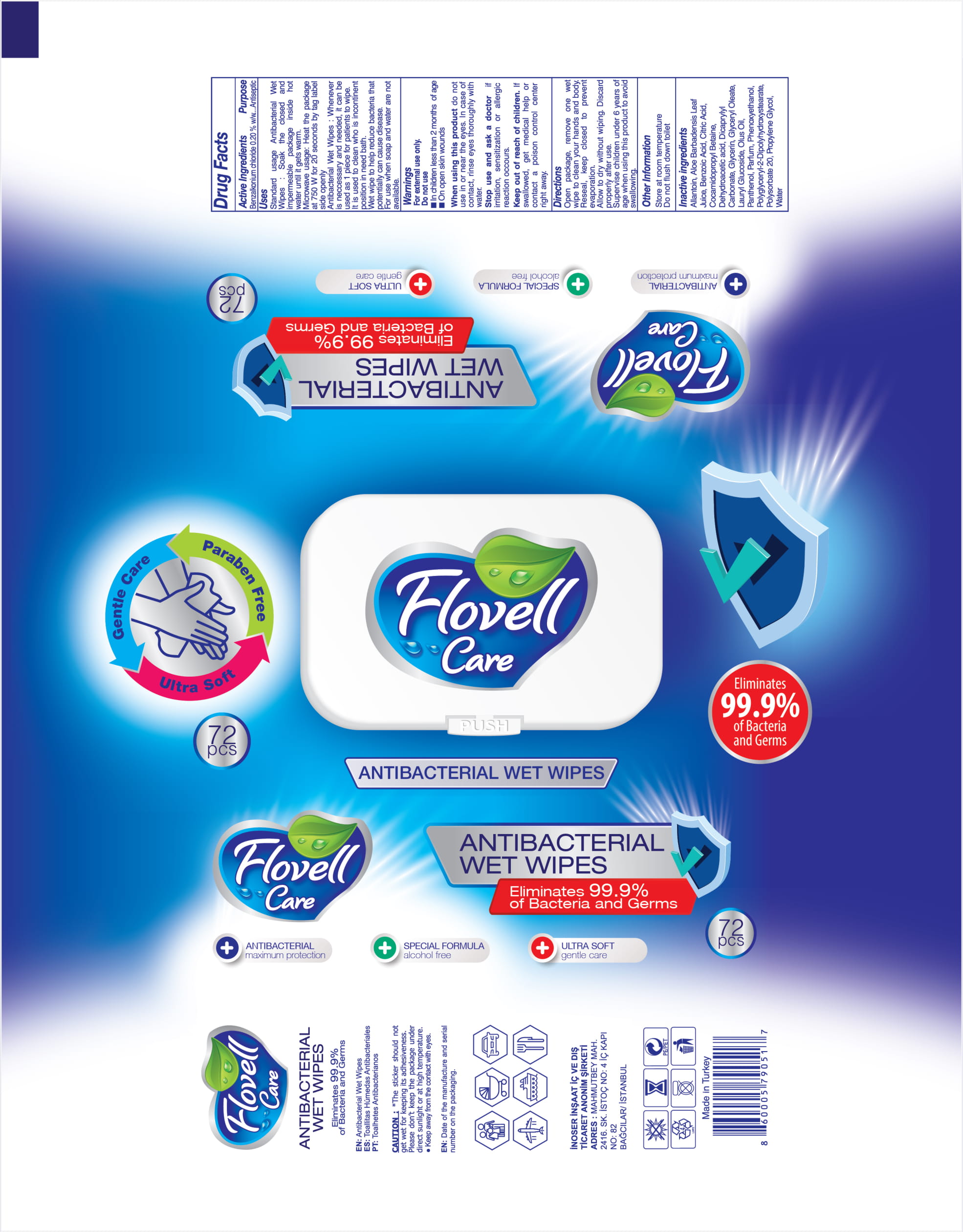 DRUG LABEL: FLOVELL CARE ANTIBACTERIAL WET WIPES
NDC: 86001-001 | Form: CLOTH
Manufacturer: INOSER INSAAT IC VE DIS TICARET ANONIM SIRKETI
Category: otc | Type: HUMAN OTC DRUG LABEL
Date: 20201206

ACTIVE INGREDIENTS: BENZALKONIUM CHLORIDE 0.2 g/100 g
INACTIVE INGREDIENTS: ALOE VERA LEAF; POLYSORBATE 20; LAURYL GLUCOSIDE; PANTHENOL; PHENOXYETHANOL; OCTADECANOIC ACID, (OCTADECYLIMINO)DI-2,1-ETHANEDIYL ESTER; PROPYLENE GLYCOL; COCAMIDOPROPYL BETAINE; DICAPRYLYL CARBONATE; FATTY-ACID AMIDE HYDROLASE 1; GLYCERIN; ALLANTOIN; WATER; BENZOIC ACID; ANHYDROUS CITRIC ACID; DEHYDROACETIC ACID; GLYCERYL OLEATE

This is a hand sanitizer manufactured according to the Temporary Policy for Preparation of Certain Alcohol-Based Hand Sanitizer Products During the Public Health Emergency (CoViD-19); Guidance for Industry.

The hand sanitizer is manufactured using only the following United States Pharmacopoeia (USP) grade ingredients in the preparation of the product (percentage in final product formulation) consistent with World Health Organization (WHO) recommendations:

1. Benzalkonium Chloride (0.2%, weight/weight (w/w))
2. GLYCERYL OLEATE
3. LAURYL GLUCOSIDE
4. PANTHENOL
5. PHENOXYETHANOL
6. OCTADECANOIC ACID, (OCTADECYLIMINO)DI-2,1-ETHANEDIYL ESTER
7. PROPYLENE GLYCOL
8. COCAMIDOPROPYL BETAINE
9. DICAPRYLYL CARBONATE
10. FATTY-ACID AMIDE HYDROLASE 1
11. GLYCERIN
12. ALLANTOIN
13. WATER
14. BENZOIC ACID
15. ANHYDROUS CITRIC ACID
16. DEHYDROACETIC ACID
17. ALOE VERA LEAF
18. POLYSORBATE 20

The firm does not add other active or inactive ingredients. Different or additional ingredients may impact the quality and potency of the product.

Active Ingredient(s)

Benzalkonium Chloride 0.2 % (w/w) Purpose: Antiseptic

Purpose

Antiseptic, Hand Sanitizer

Use

Standard usage Antibacterial Wet Wipes: Soak the closed and impermable package inside hot water until it gets warm.

Microwave usage: Heat the package at 750 W for 20 seconds by tag label side openyl.

Antibacterial wet wipes: whenever is necessary and needed, it can be used as 1 piece for patients to wipes.

It is used to celan who is incontinent position in need bath.

Wet wipes to help reduce bacteria that potentially can cause disease. For use when soap and water are not available.

Warnings

For external use only.

Do not use

- in children less than 2 months of age
- on open skin wounds

When using this product do not use in or near eyes. In case of contact with eyes, rinse eyes thoroughly with water.

Stop use and ask a doctor if irritation, sensitization or allergic reaction occurs.

Keep out of reach of children. If swallowed, get medical help or contact a Poison Control Center right away.

Directions

- Open package, remove one wet wipe to clean your hands and body. Reseal, keep closed to prevent evaporation.
- Allow to dry without wiping. Discard properly after use.
- Supervise children under 6 years of age when using this product to avoid swallowing.

Other information

- Store at room temperature.
- Do not flush down toilet.

Inactive ingredients

GLYCERYL OLEATE, LAURYL GLUCOSIDE, PANTHENOL, PHENOXYETHANOL, OCTADECANOIC ACID, (OCTADECYLIMINO)DI-2,1-ETHANEDIYL ESTER, PROPYLENE GLYCOL, COCAMIDOPROPYL BETAINE, DICAPRYLYL CARBONATE, FATTY-ACID AMIDE HYDROLASE 1, GLYCERIN, ALLANTOIN, WATER, BENZOIC ACID, ANHYDROUS CITRIC ACID, DEHYDROACETIC ACID
ALOE VERA LEAF, POLYSORBATE 20

Package Label - Principal Display Panel

72 pcs NDC: 86001-001-02

15 pcs NDC 86001-001-04

100 pcs NDC: 86001-001-06